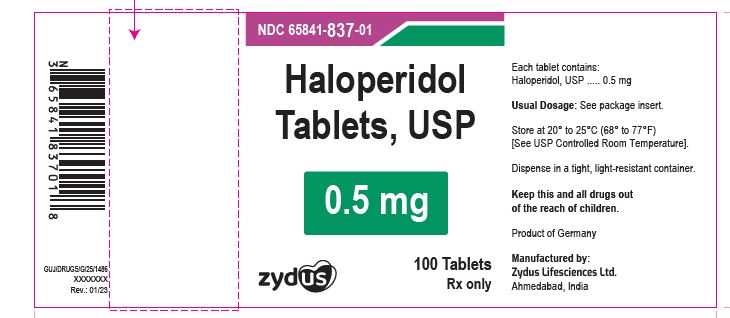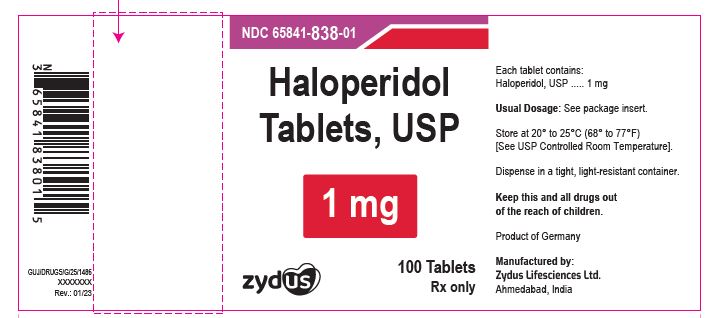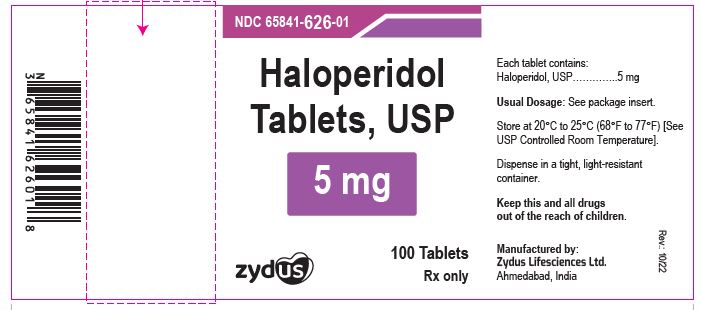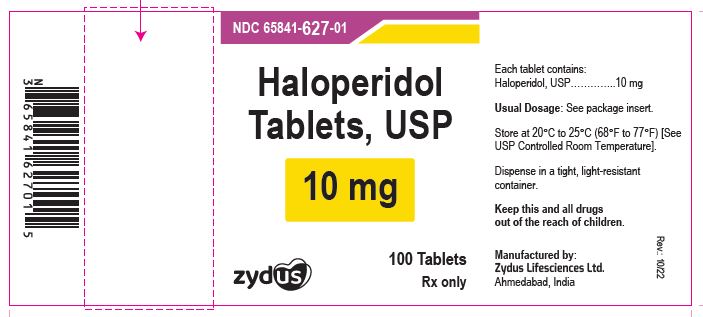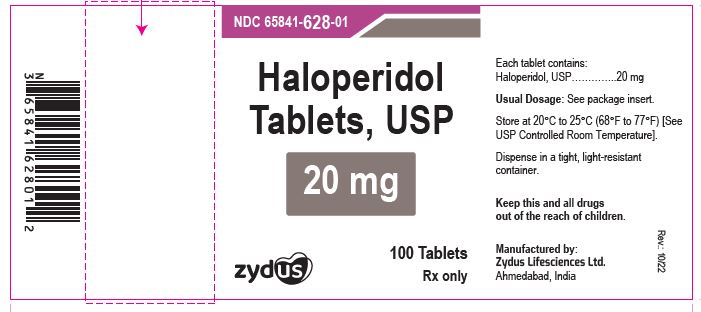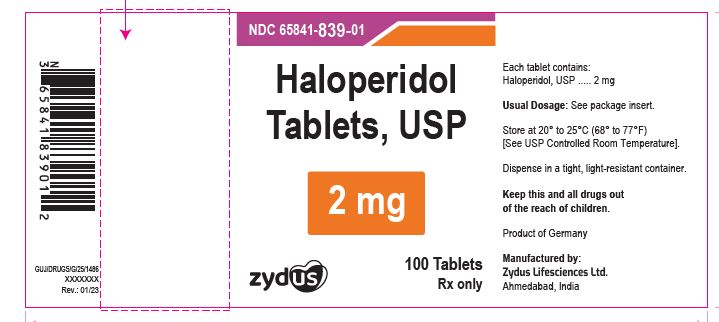 DRUG LABEL: Haloperidol
NDC: 65841-626 | Form: TABLET
Manufacturer: Zydus Lifesciences Limited
Category: prescription | Type: HUMAN PRESCRIPTION DRUG LABEL
Date: 20241130

ACTIVE INGREDIENTS: HALOPERIDOL 5 mg/1 1
INACTIVE INGREDIENTS: ALUMINUM OXIDE; CALCIUM STEARATE; D&C YELLOW NO. 10; DIBASIC CALCIUM PHOSPHATE DIHYDRATE; FD&C BLUE NO. 1 ALUMINUM LAKE; POVIDONE K30; SODIUM STARCH GLYCOLATE TYPE A POTATO; STARCH, CORN

Haloperidol Tablets, USP

PACKAGE LABEL.PRINCIPAL DISPLAY PANEL

NDC 65841-837-01 in bottle of 100 Tablets

Haloperidol Tablets USP, 0.5 mg

Rx only

100 Tablets

NDC 65841-838-01 in bottle of 100 Tablets

Haloperidol Tablets USP, 1 mg

Rx only

100 Tablets

NDC 65841-839-01 in bottle of 100 Tablets

Haloperidol Tablets USP, 2 mg

Rx only

100 Tablets

NDC 65841-626-01 in bottle of 100 Tablets

Haloperidol Tablets USP, 5 mg

Rx only

100 Tablets

NDC 65841-627-01 in bottles of 100 tablets

Haloperidol Tablets USP, 10 mg

Rx only

100 Tablets

NDC 65841-628-01 in bottles of 100 tablets

Haloperidol Tablets USP, 20 mg

Rx only

100 Tablets